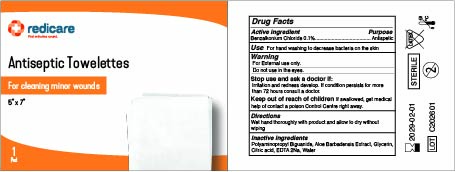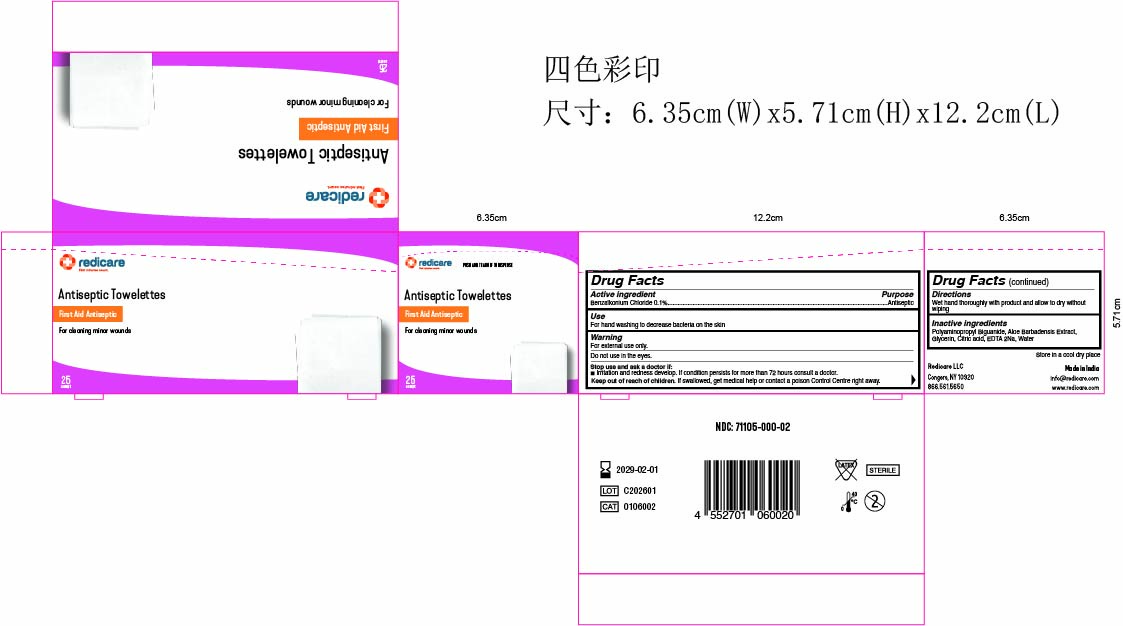 DRUG LABEL: Redicare Antiseptic Towelettes
NDC: 71105-800 | Form: CLOTH
Manufacturer: Redicare LLC
Category: otc | Type: HUMAN OTC DRUG LABEL
Date: 20260122

ACTIVE INGREDIENTS: BENZALKONIUM CHLORIDE 1 mg/1000 mg
INACTIVE INGREDIENTS: POLYAMINOPROPYL BIGUANIDE; ALOE VERA LEAF; GLYCERIN; EDETIC ACID; WATER; CITRIC ACID MONOHYDRATE

Active ingredient

Benzalkonium Chloride 0.1%

Purpose

Antiseptic

Use

For hand washing to decrease bacteria on the skin

Warning

For external use only.

Do not use

in the eyes.

Stop use and ask a doctor if:

irritation and redness develop. If condition persists for more than 72 hours consult a doctor.

Keep out of reach of children.

If swallowed, get medical help or contact poison Control Centre right away.

Directions

Wet hands thoroughly with product and allow to dry without wiping.

Inactive ingredients

Polyaminopropyl Biguanide, Aloe Barbadensis Extract, Glycerin, Citric acid, EDTA 2Na, Water